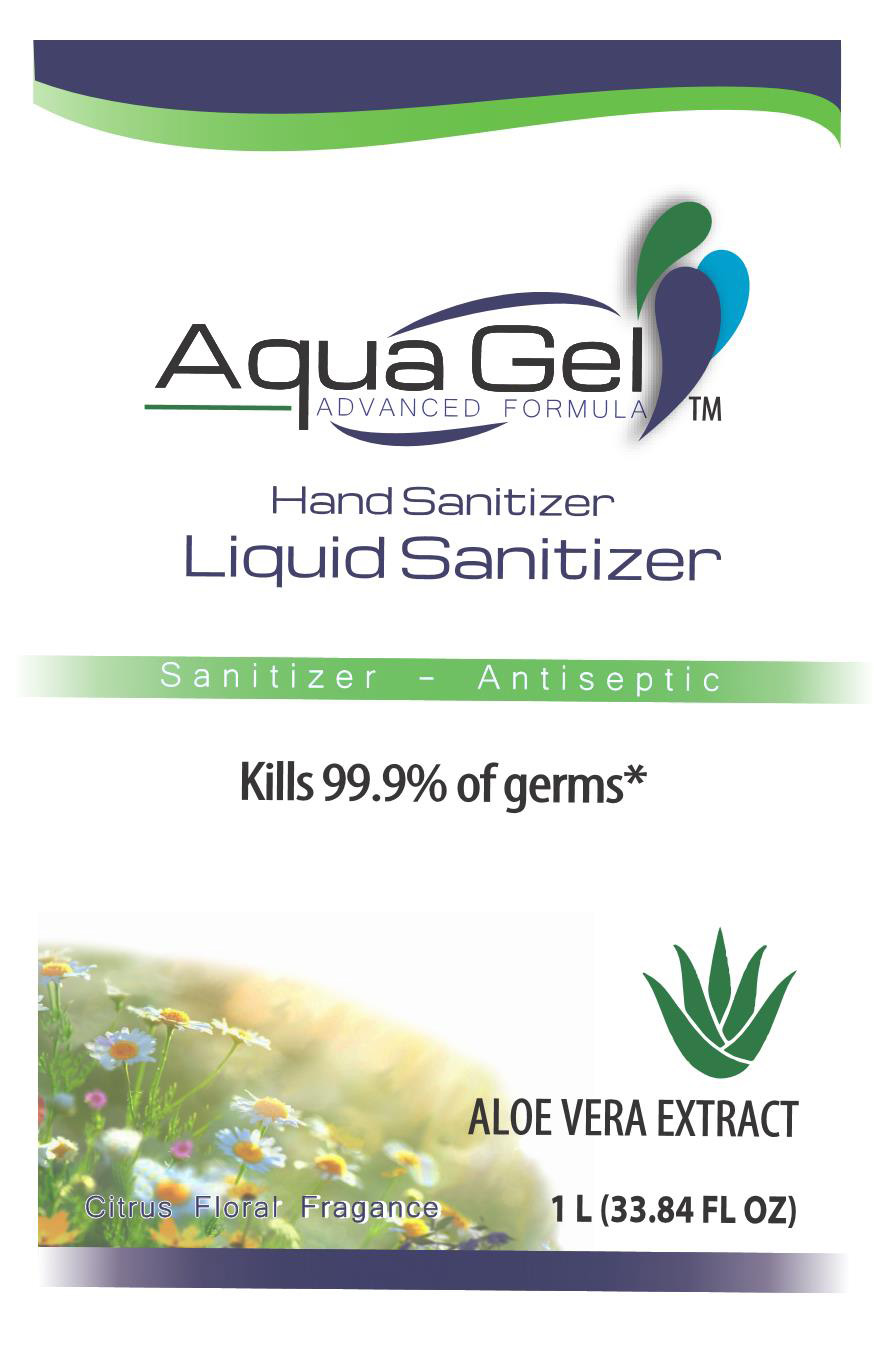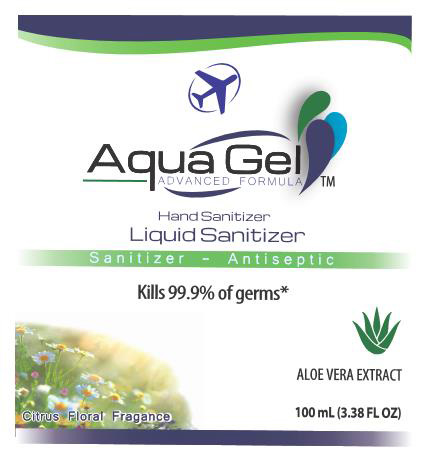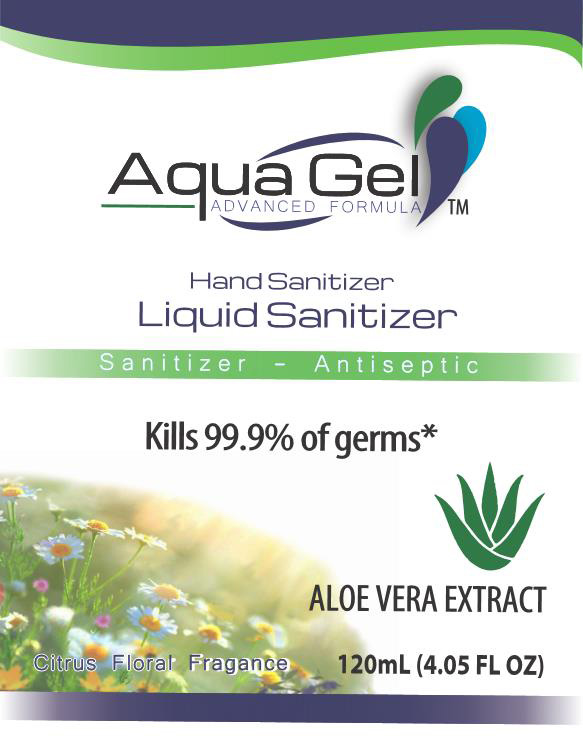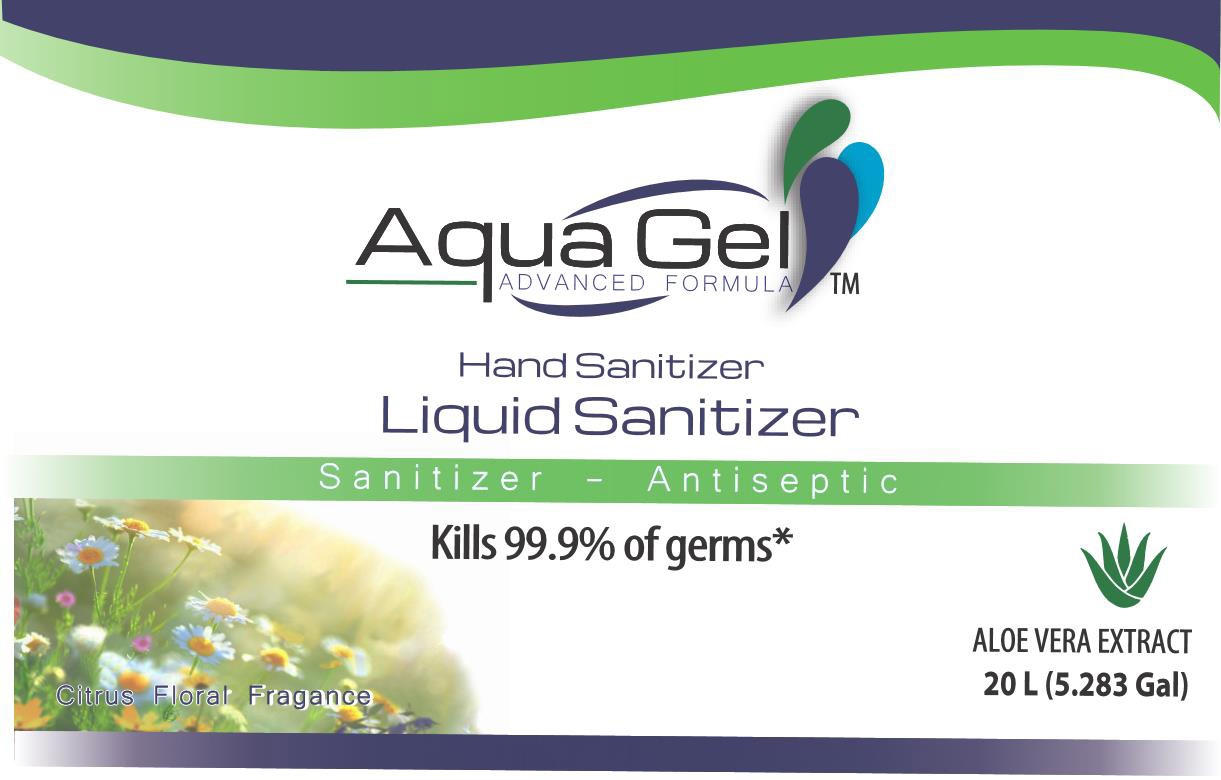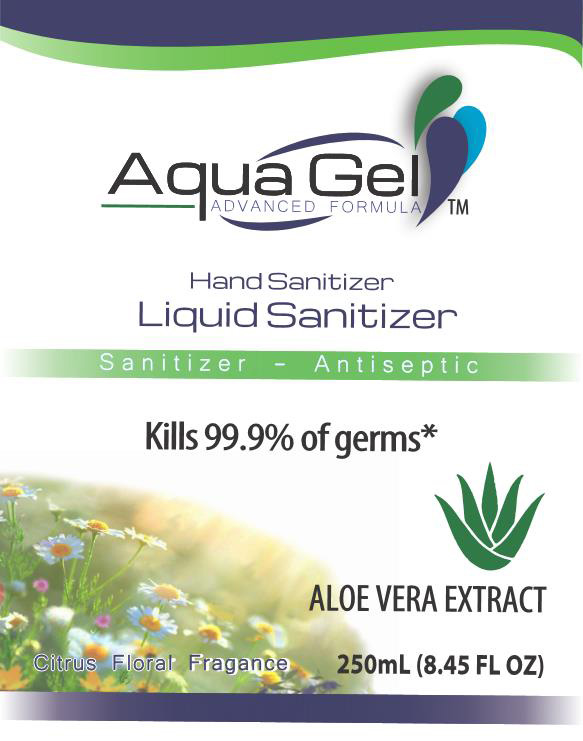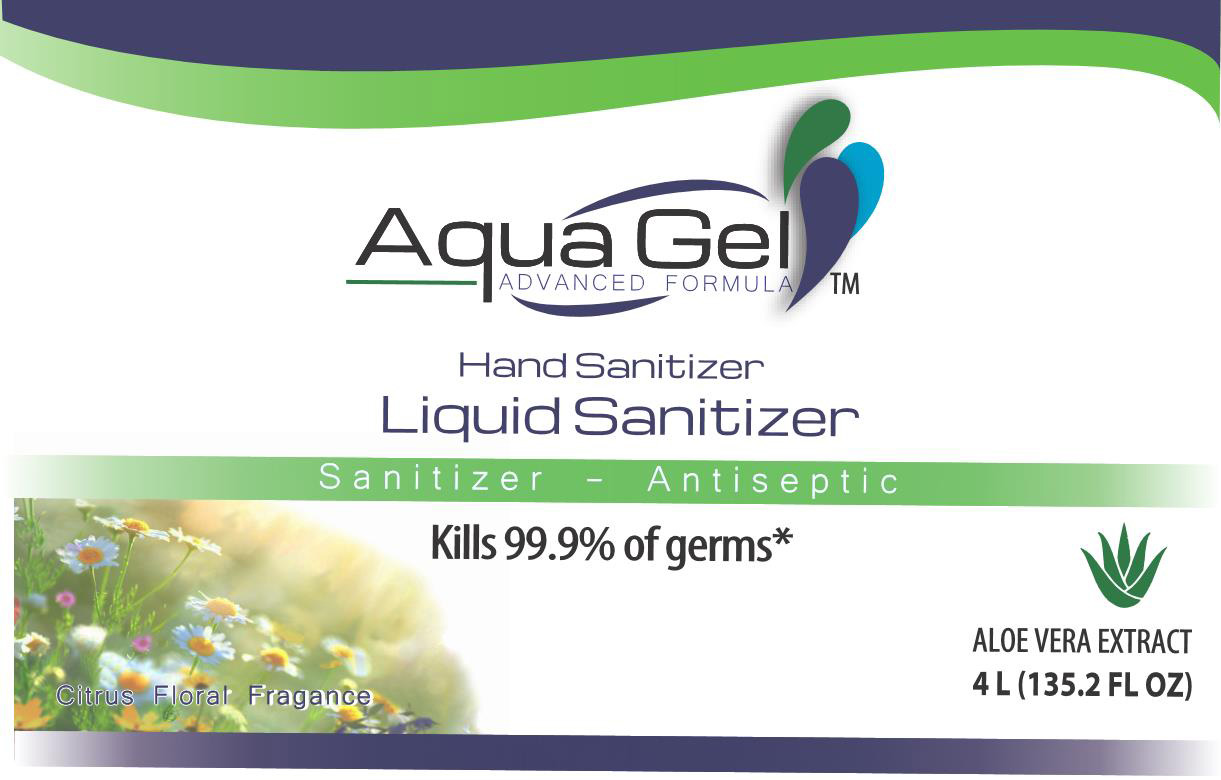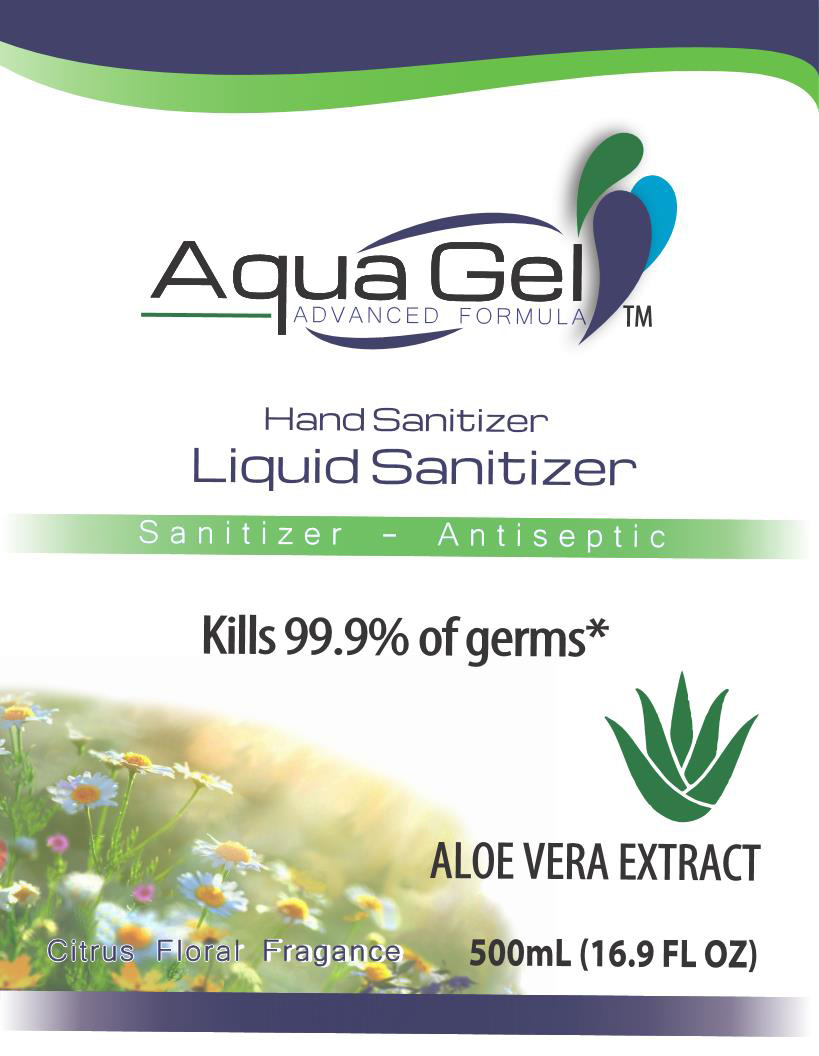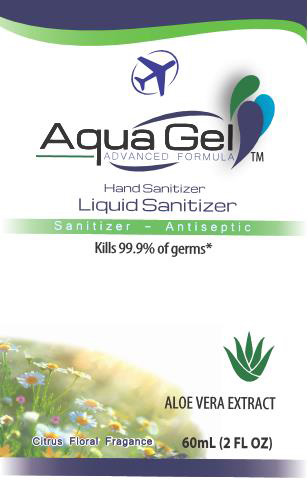 DRUG LABEL: AQUAGEL  HAND SANITIZER
NDC: 79996-400 | Form: LIQUID
Manufacturer: EPOXEMEX, S.A. DE C.V.
Category: otc | Type: HUMAN OTC DRUG LABEL
Date: 20220630

ACTIVE INGREDIENTS: ALCOHOL 70 mL/100 mL
INACTIVE INGREDIENTS: ALOE VERA LEAF; GLYCERIN; HYDROGEN PEROXIDE 0.125 mL/100 mL; WATER; TROLAMINE

AguaGel Hand Sanitizer misc

This is a hand sanitizer manufactured according to the Temporary Policy for Preparation of Certain Alcohol-Based Hand Sanitizer Products During the Public Health Emergency (CoViD-19); Guidance for Industry.

The hand sanitizer is manufactured using only the following United States Pharmacopoeia (USP) grade ingredients in the preparation of the product (percentage in final product formulation) consistent with World Health Organization (WHO) recommendations:

1. Alcohol (ethanol) (USP or Food Chemical Codex (FCC) grade) (70%, volume/volume (v/v)) in an aqueous solution denatured according to Alcohol and Tobacco Tax and Trade Bureau regulations in 27 CFR part 20.
2. Glycerol
3. Hydrogen peroxide
4. Sterile distilled water or boiled cold water
5. Aloe Vera Leaf Extract
6. Fragance
7. Triethanolamine.

The firm does not add other active or inactive ingredients. Different or additional ingredients may impact the quality and potency of the product.

Active Ingredient(s)

Alcohol 70% v/v. Purpose: Antiseptic

Purpose

Antiseptic, Hand Sanitizer

Use

Hand Sanitizer to help reduce bacteria that potentially can cause disease. For use when soap and water are not available.

Warnings

For external use only. Flammable. Keep away from heat or flame

Do not use

- in children less than 2 months of age
- on open skin wounds

When using this product keep out of eyes, ears, and mouth. In case of contact with eyes, rinse eyes thoroughly with water.
Stop use and ask a doctor if irritation or rash occurs. These may be signs of a serious condition.
Keep out of reach of children. If swallowed, get medical help or contact a Poison Control Center right away.

Stop use and ask a doctor if irritation or rash occurs. These may be signs of a serious condition.

Keep out of reach of children. If swallowed, get medical help or contact a Poison Control Center right away.

Directions

- Place enough product on hands to cover all surfaces. Rub hands together until dry.
- Supervise children under 6 years of age when using this product to avoid swallowing.

Other information

- Store between 15-30C (59-86F)
- Avoid freezing and excessive heat above 40C (104F)

Inactive ingredients

aloe vera leaf extract, fragance, glycerin, hydrogen peroxide, triethanolamine, purified water USP

Package Label - Principal Display Panel

20 L NDC: 79996-400-01

4 L NDC: 79996-400-02

1 L NDC: 79996-400-03

500 mL NDC: 79996-400-04

250 mL NDC: 79996-400-05

120 mL NDC: 79996-400-06

100 mL NDC: 79996-400-07

60 mL NDC: 79996-400-08